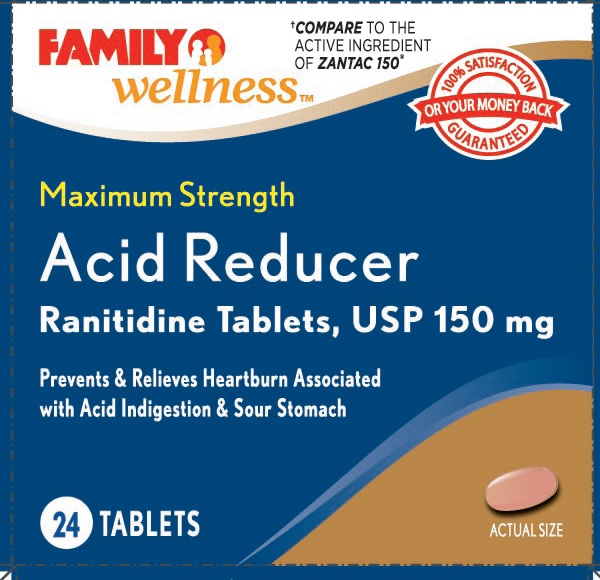 DRUG LABEL: Regular Strength Acid Reducer
NDC: 55319-351 | Form: TABLET
Manufacturer: Family Dollar
Category: otc | Type: HUMAN OTC DRUG LABEL
Date: 20141014

ACTIVE INGREDIENTS: RANITIDINE HYDROCHLORIDE 150 mg/1 1
INACTIVE INGREDIENTS: SILICON DIOXIDE; CROSCARMELLOSE SODIUM; HYPROMELLOSES; FERRIC OXIDE RED; MAGNESIUM STEARATE; CELLULOSE, MICROCRYSTALLINE; POLYETHYLENE GLYCOLS; TALC; TITANIUM DIOXIDE

Family Wellness

Active ingredient (in each tablet)

Ranitidine 150 mg
(as ranitidine hydrochloride, USP 168 mg)

Purpose

Acid reducer

Uses

- relieves heartburn associated with acid indigestion and sour stomach
- prevents heartburn associated with acid indigestion and sour stomach brought on by certain foods and beverages

Warnings

Allergy alert: Do not use if you are allergic to ranitidine or any other acid reducers

Do not use

- if you have trouble or pain swallowing food, vomiting with blood, or bloody or black stools. These may be signs of a serious condition. See your doctor
- with other acid reducers
- if you have kidney disease, except under the advice and supervision of a doctor

Ask a doctor before use if you have

- frequent chest pain
- frequent wheezing, particularly with heartburn
- unexplained weight loss
- nausea or vomiting
- stomach pain
- had heartburn over 3 months. This may be a sign of a more serious condition
- heartburn with lightheadedness, sweating, or dizziness
- chest pain or shoulder pain with shortness of breath; sweating; pain spreading to arms, neck or shoulders; or lightheadedness

Stop use and ask a doctor if

- your heartburn continues or worsens
- you need to take this product for more than 14 days

If pregnant or breast-feeding,

ask a health professional before use.

Keep out of reach of children.

In case of overdose, get medical help or contact a Poison Control Center right away (1-800-222-1222).

Directions

- adults and children 12 years and over:
  - to relieve symptoms, swallow 1 tablet with a glass of water
  - to prevent symptoms, swallow 1 tablet with a glass of water 30 to 60 minutesbefore eating food or drinking beverages that cause heartburn
  - can be used up to twice daily (do not take more than 2 tablets in 24 hours)
- children under 12 years: ask a doctor

Other information

- TAMPER EVIDENT: DO NOT USE IF THE CARTON OR INDIVIDUAL BLISTER IS OPEN OR TORN
- store at 20º - 25ºC (68º - 77ºF)
- avoid excessive heat or humidity
- this product is sodium and sugar free

Inactive ingredients

colloidal silicon dioxide, croscarmellose sodium, hyrpomellose, iron oxide red, magnesium stearate, microcrystalline cellulose, polyethylene glycol, talc, titanium dioxide

Questions

call 1-800-406-7984

Principal display panel

FAMILY
wellness

COMPARE TO THE ACTIVE INGREDIENT OF ZANTAC 150*

Maximum Strength
Acid Reducer
Ranitidine Tablets, USP 150 mg

Prevents & Relieves Heartburn Associated with Acid Indigestion & Sour Stomach

24 TABLETS

DISTRIBUTED BY
FAMILY DOLLAR SERVICES, INC.,
10401 MONROE RD,
MATTHEWS, NC 28105 USA

5110360 0614

MADE IN INDIA

Ranitidine_150mg_24's